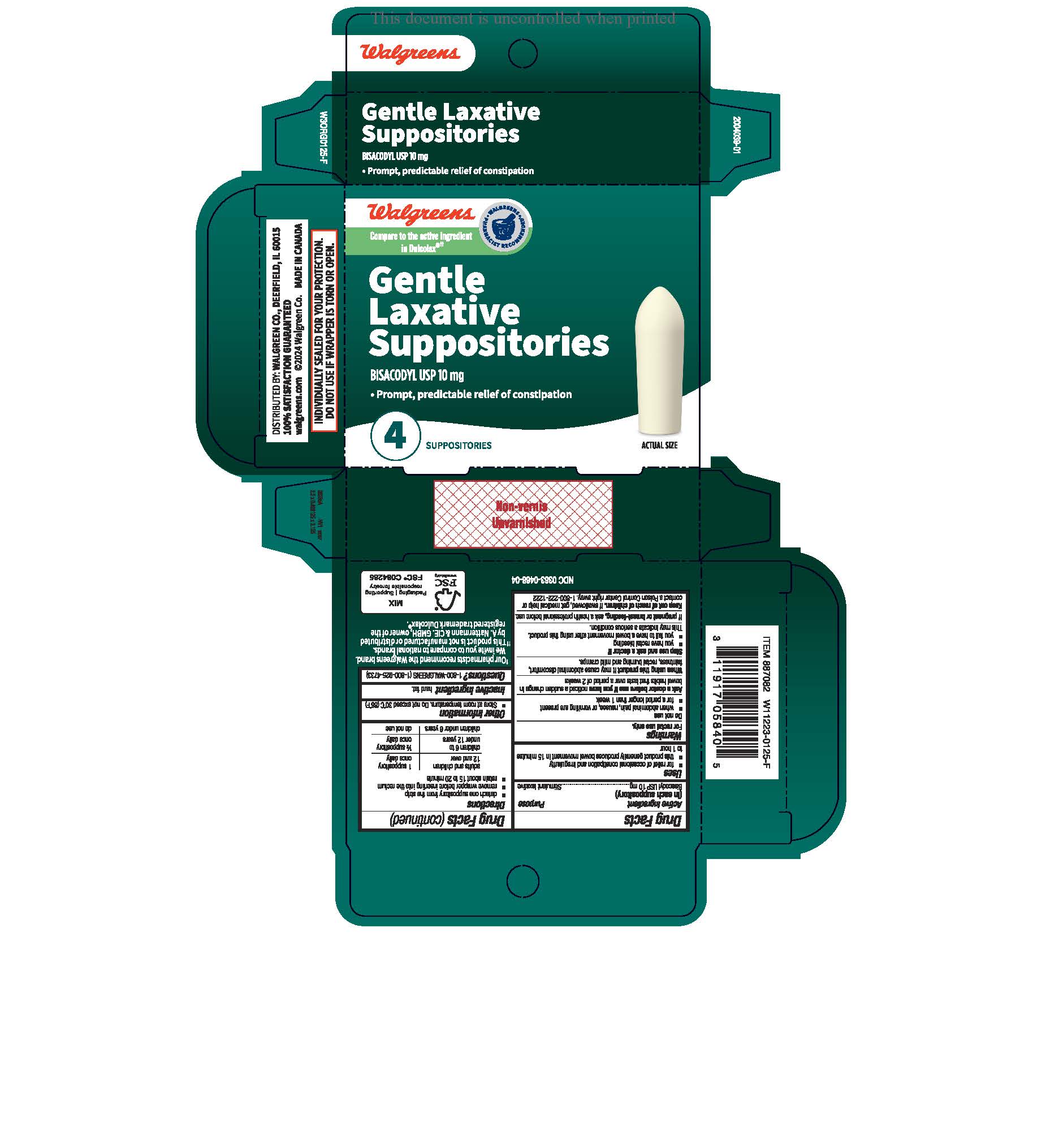 DRUG LABEL: Walgreens Gentle Laxative
NDC: 0363-0468 | Form: SUPPOSITORY
Manufacturer: Walgreens
Category: otc | Type: HUMAN OTC DRUG LABEL
Date: 20250228

ACTIVE INGREDIENTS: BISACODYL 10 mg/1 1
INACTIVE INGREDIENTS: HARD FAT

Walgreens Gentle Laxative

PURPOSE

Bisacodyl (Stimulant Laxative)

INDICATIONS AND USAGE

- for relief of occasional constipation
- this product generally produces bowel movement in 1/4 to 1 hour

WARNINGS

For rectal use only.

Do not use

- when abdominal pain, nausea, or vomiting are present
- for a period of longer than 1 week

Ask a doctor before use if you have noticed a sudden change in bowel habits that lasts
over a period of 2 weeks

When using this product it may cause abdominal discomfort, faintness, rectal burning and mild cramps

Stop use and ask a doctor if

- you have rectal bleeding
- you fail to have a bowel movement after using this product.

This may indicate a serious condition

If pregnant or breast-feeding
If pregnant or breast-feeding, ask a health professional before use.

Keep out of reach of children. If swallowed, get medical help or contact a Poison Control Center right away.

DOSAGE AND ADMINISTRATION

-detach one suppository from the strip
-remove wrapper before inserting into the rectum
adults and children 12 years of age and older: 1 suppository once daily
children 6 to under 12 years: 1/2 suppository once daily
children under 6 years: do not use

STORAGE AND HANDLING

Store at room temperature

Do not exceed 30 C (86 F)
Lot No. & Exp. Date: see wrapper or box

INACTIVE INGREDIENT

hydrogenated vegetable oil